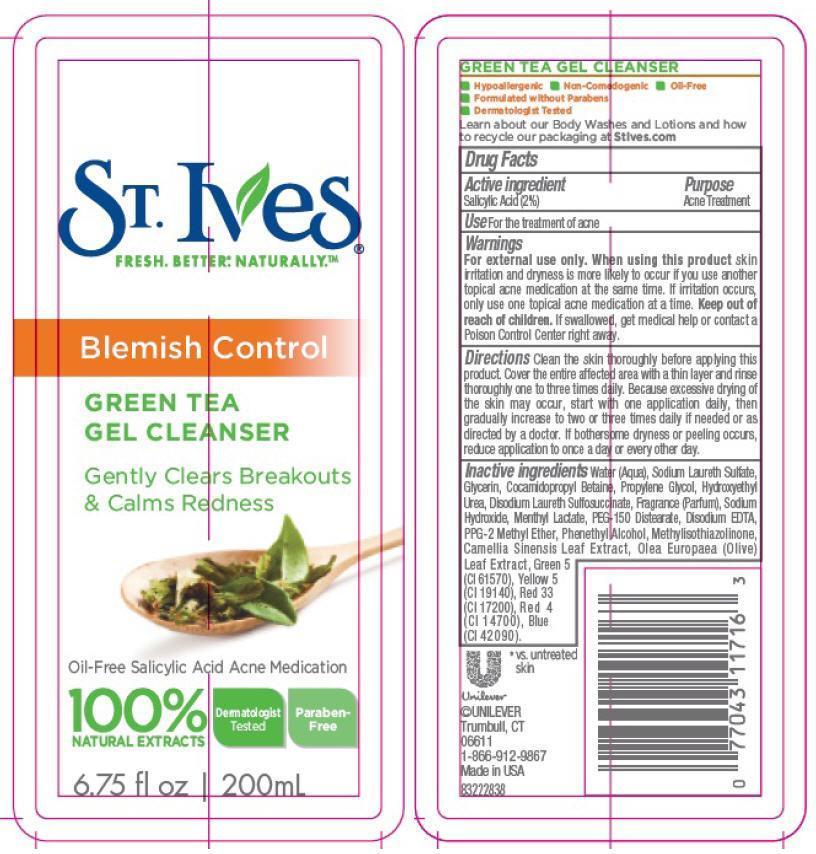 DRUG LABEL: St. Ives
NDC: 64942-1297 | Form: EMULSION
Manufacturer: CONOPCO Inc. d/b/a Unilever
Category: otc | Type: HUMAN OTC DRUG LABEL
Date: 20130430

ACTIVE INGREDIENTS: Salicylic Acid 0.02 g/1 mL
INACTIVE INGREDIENTS: WATER; SODIUM LAURETH SULFATE; GLYCERIN; COCAMIDOPROPYL BETAINE; PROPYLENE GLYCOL; HYDROXYETHYL UREA; DISODIUM LAURETH SULFOSUCCINATE; SODIUM HYDROXIDE; MENTHYL LACTATE, (-)-; PEG-150 DISTEARATE; EDETATE DISODIUM; PPG-2 METHYL ETHER; PHENYLETHYL ALCOHOL; OLEA EUROPAEA LEAF; METHYLISOTHIAZOLINONE; GREEN TEA LEAF; D&C Green No. 5; FD&C YELLOW NO. 5; D&C RED NO. 33; FD&C RED NO. 4; FD&C BLUE NO. 1

St. Ives Green Tea Gel Cleanser

Active ingredient
Salicylic Acid (2%)

Purpose
Acne Treatment

Use
For treatment of acne

Warnings
For external use only.

When using this product, skin irritation and dryness is more likely to occur if you use another topical acne medication at the same time. If irritation occurs, only use one topical acne medication at a time.

Keep out of reach of children. If swallowed, get medical help or contact a Poison Control Center right away.

DOSAGE AND ADMINISTRATION

Directions Clean the skin thoroughly before applying this product. Cover the entire affected area with a thin layer and rinse thoroughly one to three times daily. Because excessive drying of the skin may occur, start with one application daily, then gradually increase to two or three times daily if needed or as directed by a doctor. If bothersome dryness or peeling occurs, reduce application to once a day or every other day.

INACTIVE INGREDIENT

Inactive ingredientsWater (Aqua), Sodium Laureth Sulfate, Glycerin, Cocamidopropyl Betaine, Propylene Glycol, Hydroxyethyl Urea, Disodium Laureth Sulfosuccinate, Fragrance (Parfum), Sodium Hydroxide, Menthyl Lactate, PEG-150 Distearate, Disodium EDTA, PPG-2 Methyl Ether, Phenethyl Alcohol, Methylisothiazolinone, Camellia Sinensis Leaf Extract, Olea Europaea (Olive) Leaf Extract, Green 5 (CI 61570), Yellow 5 (CI 19140), Red 33 (CI 17200), Red 4 (CI 14700), Blue 1 (CI 42090)

QUESTIONS

1-866-912-9867

PACKAGE LABEL

PDP